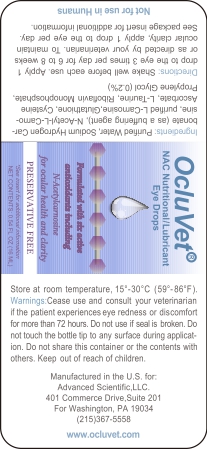 DRUG LABEL: OcluVet NAC Nutritional Lubricant Eye Drops
NDC: 86202-0090 | Form: SOLUTION/ DROPS
Manufacturer: AMBIENCE FAMILY INC
Category: animal | Type: OTC ANIMAL DRUG LABEL
Date: 20240722

ACTIVE INGREDIENTS: N-ACETYLCARNOSINE 1 mg/16 mL
INACTIVE INGREDIENTS: WATER; CARNOSINE; GLUTATHIONE; CYSTEINE; CALCIUM ASCORBATE; TAURINE; RIBOFLAVIN; RIBOFLAVIN SODIUM

OcluVet NAC Nutritional Lubricant Eye Drops

WARNINGS AND PRECAUTIONS

Not for use in humans. Keep out of reach of children. Protective gloves should be used and care should be taken when handling the product to avoid skin and eye exposure and accidental ingestion. Accidental exposure may result in skin and eye irritation. Accidental ingestion may cause gastrointestinal disturbances and hypersensitivity reactions in humans.

Warnings: Cease use and consult your veterinarian if the patient experiences eye redness or discomfort for more than 72 hours.Do not use if seal is broken. Do not touch the bottle tip to any surface during application. Do not share this container or the contents with others. Keep out of reach of children.

DOSAGE AND ADMINISTRATION

Directions: Shake well before each use.Apply drop to the eye 3 times per day for 6 to 8 weeks or as directed by your veterinarian. To maintain ocular clarity, aooly 1 drop to the eye per day. See package insert for additional information.

ACTIVE INGREDIENT

N-Acetyl-L-Carnosine

INACTIVE INGREDIENT

Ingredients: Purified Water,Sodium Hydrogen Carbonate (as a buffering agent), N-Acetyl-L-Carnosine, purifiedL Carnosine, Glutathione, Cysteine Ascorbate, L-Taurine, Riboflavin Monophosphate, PropyleneGlycol(0.2%)

WARNINGS AND PRECAUTIONS

Not for use in humans. Keep out of reach of children. Protective gloves should be used and care should be taken when handling the product to avoid skin and eye exposure and accidental ingestion. Accidental exposuremay result in skin and eye irritation. Accidental ingestion may cause gastrointestinal disturbances and hypersensitivity reactions in humans.

PACKAGE LABEL

Directions: Shake well before each use.Apply drop to the eye 3 times per day for 6 to 8 weeks or as directed by your veterinarian. To maintain ocular clarity, aooly 1 drop to the eye per day. See package insert for additional information. Ingredients: Purified Water,Sodium Hydrogen Carbonate (as a buffering agent), N-Acetyl-L-Carnosine, purifiedL Carnosine, Glutathione, Cysteine Ascorbate, L-Taurine, Riboflavin Monophosphate, PropyleneGlycol(0.2%) Warnings: Cease use and consult your veterinarian if the patient experiences eye redness or discomfort for more than 72 hours.Do not use if seal is broken. Do not touch the bottle tip to any surface during application. Do not share this container or the contents with others. Keep out of reach of children.

The labeling shows as below: